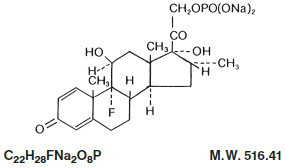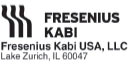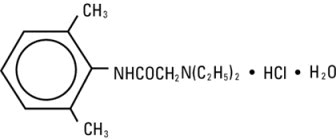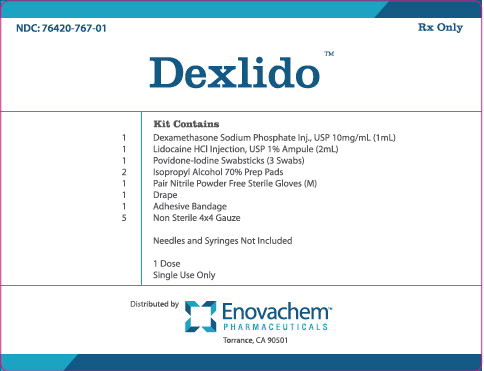 DRUG LABEL: Dexlido Kit
NDC: 76420-767 | Form: KIT | Route: INTRAMUSCULAR
Manufacturer: Asclemed USA, Inc.
Category: prescription | Type: HUMAN PRESCRIPTION DRUG LABEL
Date: 20260108

ACTIVE INGREDIENTS: DEXAMETHASONE SODIUM PHOSPHATE 10 mg/1 mL; LIDOCAINE HYDROCHLORIDE 10 mg/1 mL; POVIDONE-IODINE 10 mg/1 mL; ISOPROPYL ALCOHOL 70 mL/100 mL
INACTIVE INGREDIENTS: SODIUM CITRATE; CITRIC ACID MONOHYDRATE; SODIUM HYDROXIDE; SODIUM CHLORIDE 7 mg/1 mL; WATER; SODIUM HYDROXIDE; HYDROCHLORIC ACID; GLYCERIN; POLYSORBATE 80; SODIUM CITRATE; SODIUM PHOSPHATE, DIBASIC, ANHYDROUS; CITRIC ACID ACETATE; WATER; WATER

Dexlido Kit

Dexamethasone Sodium Phosphate Injection, USP

For Intravenous or Intramuscular Use Only

Rx only

DESCRIPTION

Dexamethasone Sodium Phosphate Injection, USP, is a water-soluble inorganic ester of dexamethasone which produces a rapid response even when injected intramuscularly.

Dexamethasone Sodium Phosphate, USP chemically is Pregna-1,4-diene-3,20-dione, 9-fluoro- 11,17-dihydroxy-16-methyl-21-(phosphonooxy)-, disodium salt, (11ß, 16α).

It occurs as a white to creamy white powder, is exceedingly hygroscopic, is soluble in water and its solutions have a pH between 7.0 and 8.5. It has the following structural formula:

Each mL of Dexamethasone Sodium Phosphate Injection, USP (Preservative Free) contains dexamethasone sodium phosphate, USP equivalent to 10 mg dexamethasone phosphate; 24.75 mg sodium citrate, dihydrate; and Water for Injection, q.s. pH adjusted with citric acid or sodium hydroxide, if necessary. pH: 7.0 to 8.5.

CLINICAL PHARMACOLOGY

Dexamethasone sodium phosphate injection has a rapid onset but short duration of action when compared with less soluble preparations. Because of this, it is suitable for the treatment of acute disorders responsive to adrenocortical steroid therapy.

Naturally occurring glucocorticoids (hydrocortisone and cortisone), which also have salt-retaining properties, are used as replacement therapy in adrenocortical deficiency states. Their synthetic analogs, including dexamethasone, are primarily used for their potent anti-inflammatory effects in disorders of many organ systems.

Glucocorticoids cause profound and varied metabolic effects. In addition, they modify the body’s immune responses to diverse stimuli.

At equipotent anti-inflammatory doses, dexamethasone almost completely lacks the sodium-retaining property of hydrocortisone and closely related derivatives of hydrocortisone.

INDICATIONS AND USAGE

By intravenous or intramuscular injection when oral therapy is not feasible:

1. Endocrine Disorders

Primary or secondary adrenocortical insufficiency (hydrocortisone or cortisone is the drug of choice; synthetic analogs may be used in conjunction with mineralocorticoids

where applicable; in infancy, mineralocorticoid supplementation is of particular importance).

Acute adrenocortical insufficiency (hydrocortisone or cortisone is the drug of choice; mineralocorticoid supplementation may be necessary, particularly when synthetic analogs

are used).

Preoperatively, and in the event of serious trauma or illness, in patients with known adrenal insufficiency or when adrenocortical reserve is doubtful.

Shock unresponsive to conventional therapy if adrenocortical insufficiency exists or is suspected.

Congenital adrenal hyperplasia

Nonsuppurative thyroiditis

Hypercalcemia associated with cancer

2. Rheumatic Disorders

As adjunctive therapy for short-term administration (to tide the patient over an acute episode or exacerbation) in:

Post-traumatic osteoarthritis

Synovitis of osteoarthritis

Rheumatoid arthritis, including juvenile rheumatoid arthritis (selected cases may require low-dose maintenance therapy).

Acute and subacute bursitis

Epicondylitis

Acute nonspecific tenosynovitis

Acute gouty arthritis

Psoriatic arthritis

Ankylosing spondylitis

3. Collagen Diseases

During an exacerbation or as maintenance therapy in selected cases of:

Systemic lupus erythematosus

Acute rheumatic carditis

4. Dermatologic Diseases

Pemphigus

Severe erythema multiforme (Stevens-Johnson syndrome)

Exfoliative dermatitis

Bullous dermatitis herpetiformis

Severe seborrheic dermatitis

Severe psoriasis

Mycosis fungoides

5. Allergic States

Control of severe or incapacitating allergic conditions intractable to adequate trials of conventional treatment in:

Bronchial asthma

Contact dermatitis

Atopic dermatitis

Serum sickness

Seasonal or perennial allergic rhinitis

Drug hypersensitivity reactions

Urticarial transfusion reactions

Acute noninfectious laryngeal edema (epinephrine is the drug of first choice).

6. Ophthalmic Diseases

Severe acute and chronic allergic and inflammatory processes involving the eye, such as:

Herpes zoster ophthalmicus

Iritis, iridocyclitis

Chorioretinitis

Diffuse posterior uveitis and choroiditis

Optic neuritis

Sympathetic ophthalmia

Anterior segment inflammation

Allergic conjunctivitis

Keratitis

Allergic corneal marginal ulcers

7. Gastrointestinal Diseases

To tide the patient over a critical period of the disease in:

Ulcerative colitis (systemic therapy)

Regional enteritis (systemic therapy)

8. Respiratory Diseases

Symptomatic sarcoidosis

Berylliosis

Fulminating or disseminated pulmonary tuberculosis when used concurrently with appropriate antituberculous chemotherapy.

Loeffler’s syndrome not manageable by other means.

Aspiration pneumonitis

9. Hematologic Disorders

Acquired (autoimmune) hemolytic anemia.

Idiopathic thrombocytopenic purpura in adults

(IV only; IM administration is contraindicated).

Secondary thrombocytopenia in adults

Erythroblastopenia (RBC anemia)

Congenital (erythroid) hypoplastic anemia

10. Neoplastic Diseases

For palliative management of:

Leukemias and lymphomas in adults

Acute leukemia of childhood

11. Edematous States

To induce diuresis or remission of proteinuria in the nephrotic syndrome, without uremia, of the idiopathic type or that due to lupus erythematosus.

12. Miscellaneous

Tuberculous meningitis with subarachnoid block or impending block when used concurrently with appropriate antituberculous chemotherapy.

Trichinosis with neurologic or myocardial involvement.

13. Diagnostic testing of adrenocortical hyperfunction.

14. Cerebral Edema associated with primary or metastatic brain tumor, craniotomy, or head injury. Use in cerebral edema is not a substitute for careful neurosurgical evaluation

and definitive management such as neurosurgery or other specific therapy.

CONTRAINDICATIONS

Systemic fungal infections (see WARNINGSregarding amphotericin B).

Hypersensitivity to any component of this product (see WARNINGS) .

WARNINGS

Because rare instances of anaphylactoid reactions have occurred in patients receiving parenteral corticosteroid therapy, appropriate precautionary measures should be taken prior to administration, especially when the patient has a history of allergy to any drug. Anaphylactoid and hypersensitivity reactions have been reported for dexamethasone sodium phosphate injection (see ADVERSE REACTIONS).

Corticosteroids may exacerbate systemic fungal infections and, therefore, should not be used in the presence of such infections unless they are needed to control drug reactions due to amphotericin B. Moreover, there have been cases reported in which concomitant use of amphotericin B and hydrocortisone was followed by cardiac enlargement and congestive failure.

In patients on corticosteroid therapy subjected to any unusual stress, increased dosage of rapidly acting corticosteroids before, during, and after the stressful situation is indicated.

Drug-induced secondary adrenocortical insufficiency may result from too rapid withdrawal of corticosteroids and may be minimized by gradual reduction of dosage. This type of relative insufficiency may persist for months after discontinuation of therapy; therefore, in any situation of stress occurring during that period, hormone therapy should be reinstituted. If the patient is receiving steroids already, dosage may have to be increased. Since mineralocorticoid secretion may be impaired, salt and/or a mineralocorticoid should be administered concurrently.

Corticosteroids may mask some signs of infection, and new infections may appear during their use. There may be decreased resistance and inability to localize infection when corticosteroids are used. Moreover, corticosteroids may affect the nitroblue-tetrazolium test for bacterial infection and produce false negative results.

In cerebral malaria, a double-blind trial has shown that the use of corticosteroids is associated with prolongation of coma and a higher incidence of pneumonia and gastrointestinal bleeding.

Corticosteroids may activate latent amebiasis. Therefore, it is recommended that latent or active amebiasis be ruled out before initiating corticosteroid therapy in any patient who has spent time in the tropics or in any patient with unexplained diarrhea.

Prolonged use of corticosteroids may produce posterior subcapsular cataracts, glaucoma with possible damage to the optic nerves, and may enhance the establishment of secondary ocular infections due to fungi or viruses.

Average and large doses of cortisone or hydrocortisone can cause elevation of blood pressure, salt and water retention, and increased excretion of potassium. These effects are less likely to occur with the synthetic derivatives except when used in large doses. Dietary salt restriction and potassium supplementation may be necessary. All corticosteroids increase calcium excretion.

Administration of live virus vaccines, including smallpox, is contraindicated in individuals receiving immunosuppressive doses of corticosteroids. If inactivated viral or bacterial vaccines are administered to individuals receiving immunosuppressive doses of corticosteroids, the expected serum antibody response may not be obtained. However, immunization procedures may be undertaken in patients who are receiving corticosteroids as replacement therapy, e.g., for Addison’s disease.

Patients who are on drugs which suppress the immune system are more susceptible to infections than healthy individuals. Chickenpox and measles, for example, can have a more serious or even fatal course in non-immune children or adults on corticosteroids. In such children or adults who have not had these diseases, particular care should be taken to avoid exposure. The risk of developing a disseminated infection varies among individuals and can be related to the dose, route and duration of corticosteroid administration as well as to the underlying disease. If exposed to chickenpox, prophylaxis with varicella zoster immune globulin (VZIG) may be indicated. If chickenpox develops, treatment with antiviral agents may be considered. If exposed to measles, prophylaxis with immune globulin (IG) may be indicated. (See the respective package inserts for VZIG and IG for complete prescribing information).

The use of dexamethasone sodium phosphate injection in active tuberculosis should be restricted to those cases of fulminating or disseminated tuberculosis in which the corticosteroid is used for the management of the disease in conjunction with an appropriate antituberculous regimen.

If corticosteroids are indicated in patients with latent tuberculosis or tuberculin reactivity, close observation is necessary as reactivation of the disease may occur. During prolonged corticosteroid therapy, these patients should receive chemoprophylaxis.

Literature reports suggest an apparent association between use of corticosteroids and left ventricular free wall rupture after a recent myocardial infarction; therefore, therapy with corticosteroids should be used with great caution in these patients.

Serious Neurologic Adverse Reactions with Epidural Administration

Serious neurologic events, some resulting in death, have been reported with epidural injection of corticosteroids. Specific events reported include, but are not limited to, spinal cord infarction, paraplegia, quadriplegia, cortical blindness, and stroke. These serious neurologic events have been reported with and without use of fluoroscopy. The safety and effectiveness of epidural administration of corticosteroids has not been established, and corticosteroids are not approved for this use.

Usage in Pregnancy

Since adequate human reproduction studies have not been done with corticosteroids, use of these drugs in pregnancy or in women of childbearing potential requires that the anticipated benefits be weighed against the possible hazards to the mother and embryo or fetus. Infants born of mothers who have received substantial doses of corticosteroids during pregnancy should be carefully observed for signs of hypoadrenalism.

Corticosteroids appear in breast milk and could suppress growth, interfere with endogenous corticosteroid production, or cause other unwanted effects. Mothers taking pharmacologic doses of corticosteroids should be advised not to nurse.

PRECAUTIONS

This product, like many other steroid formulations, is sensitive to heat. Therefore, it should not be autoclaved when it is desirable to sterilize the exterior of the vial.

Following prolonged therapy, withdrawal of corticosteroids may result in symptoms of the corticosteroid withdrawal syndrome including fever, myalgia, arthralgia, and malaise. This may occur in patients even without evidence of adrenal insufficiency.

There is an enhanced effect of corticosteroids in patients with hypothyroidism and in those with cirrhosis.

Corticosteroids should be used cautiously in patients with ocular herpes simplex for fear of corneal perforation.

The lowest possible dose of corticosteroid should be used to control the condition under treatment, and when reduction in dosage is possible, the reduction must be gradual.

Psychic derangements may appear when corticosteroids are used, ranging from euphoria, insomnia, mood swings, personality changes, and severe depression to frank psychotic manifestations. Also, existing emotional instability or psychotic tendencies may be aggravated by corticosteroids.

Aspirin should be used within caution in conjunction with corticosteroids in hypoprothrombinemia.

Steroids should be used with caution in nonspecific ulcerative colitis, if there is a probability of impending perforation, abscess, or other pyogenic infection, also in diverticulitis, fresh intestinal anastomoses, active or latent peptic ulcer, renal insufficiency, hypertension, osteoporosis, and myasthenia gravis. Signs of peritoneal irritation following gastrointestinal perforation in patients receiving large doses of corticosteroids may be minimal or absent. Fat embolism has been reported as a possible complication of hypercortisonism.

When large doses are given, some authorities advise that antacids be administered between meals to help prevent peptic ulcer.

Steroids may increase or decrease motility and number of spermatozoa in some patients.

Phenytoin, phenobarbital, ephedrine, and rifampin may enhance the metabolic clearance of corticosteroids resulting in decreased blood levels and lessened physiologic activity, thus requiring adjustment in corticosteroid dosage. These interactions may interfere with dexamethasone suppression tests which should be interpreted with caution during administration of these drugs.

False negative results in the dexamethasone suppression test (DST) in patients being treated with indomethacin have been reported. Thus, results of the DST should be interpreted with caution in these patients.

The prothrombin time should be checked frequently in patients who are receiving corticosteroids and coumarin anticoagulants at the same time because of reports that corticosteroids have altered the response to these anticoagulants. Studies have shown that the usual effect produced by adding corticosteroids is inhibition of response to coumarins, although there have been some conflicting reports of potentiation not substantiated by studies.

When corticosteroids are administered concomitantly with potassium-depleting diuretics, patients should be observed closely for development of hypokalemia.

The slower rate of absorption by intramuscular administration should be recognized.

Information for Patients

Susceptible patients who are on immunosuppressant doses of corticosteroids should be warned to avoid exposure to chickenpox or measles. Patients should also be advised that if they are exposed, medical advice should be sought without delay.

Pediatric Use

Growth and development of infants and children patients on prolonged corticosteroid therapy should be carefully followed.

ADVERSE REACTIONS

Fluid and electrolyte disturbances:

Sodium retention

Fluid retention

Congestive heart failure in susceptible patients

Potassium loss

Hypokalemic alkalosis

Hypertension

Musculoskeletal:

Muscle weakness

Steroid myopathy

Loss of muscle mass

Osteoporosis

Vertebral compression fractures

Aseptic necrosis of femoral and humeral heads

Tendon rupture

Pathologic fracture of long bones

Gastrointestinal:

Peptic ulcer with possible subsequent perforation and hemorrhage

Perforation of the small and large bowel; particularly in patients with inflammatory

bowel disease

Pancreatitis

Abdominal distention

Ulcerative esophagitis

Dermatologic:

Impaired wound healing

Thin fragile skin

Petechiae and ecchymoses

Erythema

Increased sweating

May suppress reactions to skin tests

Burning or tingling, especially in the perineal area (after IV injection)

Other cutaneous reactions, such as allergic dermatitis, urticaria, angioneurotic edema

Neurologic:

Convulsions

Increased intracranial pressure with papilledema (pseudotumor cerebri) usually after

treatment

Vertigo

Headache

Psychic disturbances

Endocrine:

Menstrual irregularities

Development of cushingoid state

Suppression of growth in pediatric patients

Secondary adrenocortical and pituitary unresponsiveness, particularly in times of

stress, as in trauma, surgery, or illness

Decreased carbohydrate tolerance

Manifestations of latent diabetes mellitus

Increased requirements for insulin or oral hypoglycemic agents in diabetics

Hirsutism

Ophthalmic:

Posterior subcapsular cataracts

Increased intraocular pressure

Glaucoma

Exophthalmos

Retinopathy of prematurity

Metabolic:

Negative nitrogen balance due to protein catabolism

Cardiovascular:

Myocardial rupture following recent myocardial infarction (see WARNINGS)

Hypertrophic cardiomyopathy in low birth weight infants

Other:

Anaphylactoid or hypersensitivity reactions

Thromboembolism

Weight gain

Increased appetite

Nausea

Malaise

Hiccups

The following additional adverse reactions are related to parenteral corticosteroid therapy:

Hyperpigmentation or hypopigmentation

Subcutaneous and cutaneous atrophy

Sterile abscess

Charcot-like arthropathy

OVERDOSAGE

Reports of acute toxicity and/or death following overdosage of glucocorticoids are rare. In the event of overdosage, no specific antidote is available; treatment is supportive and symptomatic.

The oral LD50 of dexamethasone in female mice was 6.5 g/kg. The intravenous LD50 of dexamethasone sodium phosphate in female mice was 794 mg/kg.

DOSAGE AND ADMINISTRATION

Dexamethasone sodium phosphate injection, 10 mg/mL– For intravenous and intramuscular injection only.

Dexamethasone sodium phosphate injection can be given directly from the vial, or it can be added to Sodium Chloride Injection or Dextrose Injection and administered by intravenous drip.

Solutions used for intravenous administration or further dilution of this product should be preservative free when used in the neonate, especially the premature infant.

When it is mixed with an infusion solution, sterile precautions should be observed. Since infusion solutions generally do not contain preservatives, mixtures should be used within 24 hours.

DOSAGE REQUIREMENTS ARE VARIABLE AND MUST BE INDIVIDUALIZED ON THE BASIS OF THE DISEASE AND THE RESPONSE OF THE PATIENT.

Intravenous and Intramuscular Injection

The initial dosage of dexamethasone sodium phosphate injection varies from 0.5 to 9 mg a day depending on the disease being treated. In less severe diseases doses lower than 0.5 mg may suffice, while in severe diseases doses higher than 9 mg may be required.

The initial dosage should be maintained or adjusted until the patient’s response is satisfactory. If a satisfactory clinical response does not occur after a reasonable period of time, discontinue dexamethasone sodium phosphate injection and transfer the patient to other therapy.

After a favorable initial response, the proper maintenance dosage should be determined by decreasing the initial dosage in small amounts to the lowest dosage that maintains an adequate clinical response.

Patients should be observed closely for signs that might require dosage adjustment, including changes in clinical status resulting from remissions or exacerbations of the disease, individual drug responsiveness, and the effect of stress (e.g., surgery, infection, trauma). During stress it may be necessary to increase dosage temporarily.

If the drug is to be stopped after more than a few days of treatment, it usually should be withdrawn gradually.

When the intravenous route of administration is used, dosage usually should be the same as the oral dosage. In certain overwhelming, acute, life-threatening situations, however, administration in dosages exceeding the usual dosages may be justified and may be in multiples of the oral dosages. The slower rate of absorption by intramuscular administration should be recognized.

Shock

There is a tendency in current medical practice to use high (pharmacologic) doses of corticosteroids for the treatment of unresponsive shock. The following dosages of dexamethasone sodium phosphate injection have been suggested by various authors:

Author | Dosage
Cavanagh^1 | 3 mg/kg of body weight per 24 hours by constant intravenous infusion after an initial intravenous injection of 20 mg
Dietzman^2 | 2 to 6 mg/kg of body weight as a single intravenous injection
Frank^3 | 40 mg initially followed by repeat intravenous injection every 4 to 6 hours while shock persists
Oaks^4 | 40 mg initially followed by repeat intravenous injection every 2 to 6 hours while shock persists
Schumer^5 | 1 mg/kg of body weight as a single intravenous injection

Administration of high dose corticosteroid therapy should be continued only until the patient’s condition has stabilized and usually not longer than 48 to 72 hours.

Although adverse reactions associated with high dose, short-term corticosteroid therapy are uncommon, peptic ulceration may occur.

Cerebral Edema

Dexamethasone sodium phosphate injection is generally administered initially in a dosage of 10 mg intravenously followed by four mg every six hours intramuscularly until the symptoms of cerebral edema subside. Response is usually noted within 12 to 24 hours and dosage may be reduced after two to four days and gradually discontinued over a period of five to seven days. For palliative management of patients with recurrent or inoperable brain tumors, maintenance therapy with 2 mg two or three times a day may be effective.

Acute Allergic Disorders

In acute, self-limited allergic disorders or acute exacerbations of chronic allergic disorders, the following dosage schedule combining parenteral and oral therapy is suggested:

Dexamethasone sodium phosphate injection, first day, 4 or 8 mg intramuscularly.

Dexamethasone tablets, 0.75 mg: second and third days, 4 tablets in two divided doses each day; fourth day, 2 tablets in two divided doses; fifth and sixth days, 1 tablet each day; seventh day, no treatment; eighth day, follow-up visit.

This schedule is designed to ensure adequate therapy during acute episodes, while minimizing the risk of overdosage in chronic cases.

Parenteral drug products should be inspected visually for particulate matter and discoloration prior to administration, whenever the solution and container permit.

HOW SUPPLIED

Dexamethasone Sodium Phosphate Injection, USP (Preservative Free) equivalent to 10 mg dexamethasone phosphate, is supplied in a single dose vial as follows:

Product; No. | NDC; No. | Strength | Vial Size
500601 | 63323-506-01 | 10 mg per mL | 1 mL vial, packaged in twenty-fives.

This container closure is not made with natural rubber latex.

Storage

Store at 20° to 25°C (68° to 77°F) [see USP Controlled Room Temperature]. Sensitive to heat. Do not autoclave.

Protect from freezing.

Protect from light.

Single dose vials–Store in container until time of use. Discard unused portion.

REFERENCES

1. Cavanagh, D.; Singh, K.B.: Endotoxin shock in pregnancy and abortion, in: “Corticosteroids in the Treatment of Shock”, Schumer, W.; Nyhus, L.M., Editors, Urbana, University of Illinois Press, 1970, pp. 86-96.
2. Dietzman, R.H.; Ersek, R.A.; Bloch, J.M.; Lilleheir, R.C.: High-output, low-resistance gram-negative septic shock in man, Angiology 20: 691-700, Dec. 1969.
3. Frank, E.: Clinical observations in shock and management (in: Shields, T.F., ed.: Symposium on current concepts and management of shock), J. Maine Med. Ass. 59: 195-200, Oct. 1968.
4. Oaks, W. W.; Cohen, H.E.: Endotoxin shock in the geriatric patient, Geriat. 22: 120-130, Mar. 1967.
5. Schumer, W.; Nyhus, L.M.: Corticosteroid effect on biochemical parameters of human oligemic shock, Arch. Surg. 100: 405-408, Apr. 1970.

45955E

Revised: May 2014

Lidocaine Hydrochloride Injection, USP

For Infiltration and Nerve Block

Rx only

DESCRIPTION

Lidocaine hydrochloride injection, USP is sterile, nonpyrogenic, aqueous solution that contains a local anesthetic agent and is administered parenterally by injection. See INDICATIONS AND USAGE section for specific uses.
Lidocaine hydrochloride injection, USP contains lidocaine hydrochloride, which is chemically designated as acetamide, 2-(diethylamino)-N-(2,6-dimethylphenyl)-, monohydrochloride and has the molecular weight 270.8. Lidocaine hydrochloride (C14H22N2O • HCl) has the following structural formula:

Lidocaine hydrochloride injection, USP is a sterile, nonpyrogenic, isotonic solution containing sodium chloride. The pH of the solution is adjusted to approximately 6.5 (5.0 to 7.0) with sodium hydroxide and/or hydrochloric acid.

CLINICAL PHARMACOLOGY

Mechanism of Action

Lidocaine stabilizes the neuronal membrane by inhibiting the ionic fluxes required for the initiation and conduction of impulses thereby effecting local anesthetic action.

Hemodynamics

Excessive blood levels may cause changes in cardiac output, total peripheral resistance, and mean arterial pressure. With central neural blockade these changes may be attributable to block of autonomic fibers, a direct depressant effect of the local anesthetic agent on various components of the cardiovascular system, and/or the beta-adrenergic receptor stimulating action of epinephrine when present. The net effect is normally a modest hypotension when the recommended dosages are not exceeded.

Pharmacokinetics and Metabolism

Information derived from diverse formulations, concentrations and usages reveals that lidocaine is completely absorbed following parenteral administration, its rate of absorption depending, for example, upon various factors such as the site of administration and the presence or absence of a vasoconstrictor agent. Except for intravascular administration, the highest blood levels are obtained following intercostal nerve block and the lowest after subcutaneous administration.
The plasma binding of lidocaine is dependent on drug concentration, and the fraction bound decreases with increasing concentration. At concentrations of 1 to 4 mcg of free base per mL 60 to 80 percent of lidocaine is protein bound. Binding is also dependent on the plasma concentration of the alpha-1-acid glycoprotein.
Lidocaine crosses the blood-brain and placental barriers, presumably by passive diffusion.
Lidocaine is metabolized rapidly by the liver, and metabolites and unchanged drug are excreted by the kidneys. Biotransformation includes oxidative N-dealkylation, ring hydroxylation, cleavage of the amide linkage, and conjugation. N-dealkylation, a major pathway of biotransformation, yields the metabolites monoethylglycinexylidide and glycinexylidide. The pharmacological/toxicological actions of these metabolites are similar to, but less potent than, those of lidocaine. Approximately 90% of lidocaine administered is excreted in the form of various metabolites, and less than 10% is excreted unchanged. The primary metabolite in urine is a conjugate of 4-hydroxy-2,6-dimethylaniline.
The elimination half-life of lidocaine following an intravenous bolus injection is typically 1.5 to 2 hours. Because of the rapid rate at which lidocaine is metabolized, any condition that affects liver function may alter lidocaine kinetics. The half-life may be prolonged two-fold or more in patients with liver dysfunction. Renal dysfunction does not affect lidocaine kinetics but may increase the accumulation of metabolites.
Factors such as acidosis and the use of CNS stimulants and depressants affect the CNS levels of lidocaine required to produce overt systemic effects. Objective adverse manifestations become increasingly apparent with increasing venous plasma levels above 6 mcg free base per mL. In the rhesus monkey arterial blood levels of 18 to 21 mcg/mL have been shown to be threshold for convulsive activity.

INDICATIONS AND USAGE

Lidocaine hydrochloride injection is indicated for production of local or regional anesthesia by infiltration techniques such as percutaneous injection and intravenous regional anesthesia by peripheral nerve block techniques such as brachial plexus and intercostal and by central neural techniques such as lumbar and caudal epidural blocks, when the accepted procedures for these techniques as described in standard textbooks are observed.

CONTRAINDICATIONS

Lidocaine hydrochloride is contraindicated in patients with a known history of hypersensitivity to local anesthetics of the amide type.

WARNINGS

LIDOCAINE HYDROCHLORIDE INJECTION FOR INFILTRATION AND NERVE BLOCK SHOULD BE EMPLOYED ONLY BY CLINICIANS WHO ARE WELL VERSED IN DIAGNOSIS AND MANAGEMENT OF DOSE-RELATED TOXICITY AND OTHER ACUTE EMERGENCIES THAT MIGHT ARISE FROM THE BLOCK TO BE EMPLOYED AND THEN ONLY AFTER ENSURING THE IMMEDIATE AVAILABILITY OF OXYGEN, OTHER RESUSCITATIVE DRUGS, CARDIOPULMONARY EQUIPMENT AND THE PERSONNEL NEEDED FOR PROPER MANAGEMENT OF TOXIC REACTIONS AND RELATED EMERGENCIES (see also ADVERSE REACTIONSand PRECAUTIONS). DELAY IN PROPER MANAGEMENT OF DOSE-RELATED TOXICITY, UNDERVENTILATION FROM ANY CAUSE AND/OR ALTERED SENSITIVITY MAY LEAD TO THE DEVELOPMENT OF ACIDOSIS, CARDIAC ARREST AND, POSSIBLY, DEATH.
Methemoglobinemia
Cases of methemoglobinemia have been reported in association with local anesthetic use. Although all patients are at risk for methemoglobinemia, patients with glucose-6-phosphate dehydrogenase deficiency, congenital or idiopathic methemoglobinemia, cardiac or pulmonary compromise, infants under 6 months of age, and concurrent exposure to oxidizing agents or their metabolites are more susceptible to developing clinical manifestations of the condition. If local anesthetics must be used in these patients, close monitoring for symptoms and signs of methemoglobinemia is recommended.
Signs of methemoglobinemia may occur immediately or may be delayed some hours after exposure, and are characterized by a cyanotic skin discoloration and/or abnormal coloration of the blood. Methemoglobin levels may continue to rise; therefore, immediate treatment is required to avert more serious central nervous system and cardiovascular adverse effects, including seizures, coma, arrhythmias, and death. Discontinue lidocaine hydrochloride and any other oxidizing agents. Depending on the severity of the signs and symptoms, patients may respond to supportive care, i.e., oxygen therapy, hydration. A more severe clinical presentation may require treatment with methylene blue, exchange transfusion, or hyperbaric oxygen.
Intra-articular infusions of local anesthetics following arthroscopic and other surgical procedures is an unapproved use, and there have been postmarketing reports of chondrolysis in patients receiving such infusions. The majority of reported cases of chondrolysis have involved the shoulder joint; cases of gleno-humeral chondrolysis have been described in pediatric and adult patients following intra-articular infusions of local anesthetics with and without epinephrine for periods of 48 to 72 hours. There is insufficient information to determine whether shorter infusion periods are not associated with these findings. The time of onset of symptoms, such as joint pain, stiffness and loss of motion can be variable, but may begin as early as the 2nd month after surgery. Currently, there is no effective treatment for chondrolysis; patients who experienced chondrolysis have required additional diagnostic and therapeutic procedures and some required arthroplasty or shoulder replacement.
To avoid intravascular injection, aspiration should be performed before the local anesthetic solution is injected. The needle must be repositioned until no return of blood can be elicited by aspiration. Note, however, that the absence of blood in the syringe does not guarantee that intravascular injection has been avoided.
Anaphylactic reactions may occur following administration of lidocaine hydrochloride (see ADVERSE REACTIONS).
In the case of severe reaction, discontinue the use of the drug.

PRECAUTIONS

General

The safety and effectiveness of lidocaine hydrochloride depend on proper dosage, correct technique, adequate precautions, and readiness for emergencies. Standard textbooks should be consulted for specific techniques and precautions for various regional anesthetic procedures.
Resuscitative equipment, oxygen, and other resuscitative drugs should be available for immediate use (see WARNINGSand ADVERSE REACTIONS). The lowest dosage that results in effective anesthesia should be used to avoid high plasma levels and serious adverse effects. Syringe aspirations should also be performed before and during each supplemental injection when using indwelling catheter techniques. During the administration of epidural anesthesia, it is recommended that a test dose be administered initially and that the patient be monitored for central nervous system toxicity and cardiovascular toxicity, as well as for signs of unintended intrathecal administration, before proceeding. When clinical conditions permit, consideration should be given to employing local anesthetic solutions that contain epinephrine for the test dose because circulatory changes compatible with epinephrine may also serve as a warning sign of unintended intravascular injection. An intravascular injection is still possible even if aspirations for blood are negative. Repeated doses of lidocaine hydrochloride may cause significant increases in blood levels with each repeated dose because of slow accumulation of the drug or its metabolites. Tolerance to elevated blood levels varies with the status of the patient. Debilitated, elderly patients, acutely ill patients, and children should be given reduced doses commensurate with their age and physical condition. Lidocaine hydrochloride should also be used with caution in patients with severe shock or heart block.
Lumbar and caudal epidural anesthesia should be used with extreme caution in persons with the following conditions: existing neurological disease, spinal deformities, septicemia, and severe hypertension.
Local anesthetic solutions containing a vasoconstrictor should be used cautiously and in carefully circumscribed quantities in areas of the body supplied by end arteries or having otherwise compromised blood supply. Patients with peripheral vascular disease and those with hypertensive vascular disease may exhibit exaggerated vasoconstrictor response. Ischemic injury or necrosis may result. Preparations containing a vasoconstrictor should be used with caution in patients during or following the administration of potent general anesthetic agents, since cardiac arrhythmias may occur under such conditions.
Careful and constant monitoring of cardiovascular and respiratory (adequacy of ventilation) vital signs and the patient’s state of consciousness should be accomplished after each local anesthetic injection. It should be kept in mind at such times that restlessness, anxiety, tinnitus, dizziness, blurred vision, tremors, depression or drowsiness may be early warning signs of central nervous system toxicity.
Since amide-type local anesthetics are metabolized by the liver, lidocaine hydrochloride injection should be used with caution in patients with hepatic disease. Patients with severe hepatic disease, because of their inability to metabolize local anesthetics normally, are at greater risk of developing toxic plasma concentrations. Lidocaine hydrochloride injection should also be used with caution in patients with impaired cardiovascular function since they may be less able to compensate for functional changes associated with the prolongation of A-V conduction produced by these drugs.
Many drugs used during the conduct of anesthesia are considered potential triggering agents for familial malignant hyperthermia. Since it is not known whether amide-type local anesthetics may trigger this reaction and since the need for supplemental general anesthesia cannot be predicted in advance, it is suggested that a standard protocol for the management of malignant hyperthermia should be available. Early unexplained signs of tachycardia, tachypnea, labile blood pressure and metabolic acidosis may precede temperature elevation. Successful outcome is dependent on early diagnosis, prompt discontinuance of the suspect triggering agent(s) and institution of treatment, including oxygen therapy, indicated supportive measures and dantrolene (consult dantrolene sodium intravenous package insert before using).
Proper tourniquet technique, as described in publications and standard textbooks, is essential in the performance of intravenous regional anesthesia. Solutions containing epinephrine or other vasoconstrictors should not be used for this technique.
Lidocaine hydrochloride should be used with caution in persons with known drug sensitivities. Patients allergic to para-aminobenzoic acid derivatives (procaine, tetracaine, benzocaine, etc.) have not shown cross sensitivity to lidocaine hydrochloride.

Use in the Head and Neck Area

Small doses of local anesthetics injected into the head and neck area, including retrobulbar, dental and stellate ganglion blocks, may produce adverse reactions similar to systemic toxicity seen with unintentional intravascular injections of larger doses. Confusion, convulsions, respiratory depression and/or respiratory arrest, and cardiovascular stimulation or depression have been reported. These reactions may be due to intra-arterial injection of the local anesthetic with retrograde flow to the cerebral circulation. Patients receiving these blocks should have their circulation and respiration monitored and be constantly observed. Resuscitative equipment and personnel for treating adverse reactions should be immediately available. Dosage recommendations should not be exceeded (see DOSAGE AND ADMINISTRATION).

Information for Patients

When appropriate, patients should be informed in advance that they may experience temporary loss of sensation and motor activity, usually in the lower half of the body, following proper administration of epidural anesthesia.
Inform patients that use of local anesthetics may cause methemoglobinemia, a serious condition that must be treated promptly. Advise patients or caregivers to seek immediate medical attention if they or someone in their care experience the following signs or symptoms: pale, gray, or blue colored skin (cyanosis); headache; rapid heart rate; shortness of breath; lightheadedness; or fatigue.

Clinically Significant Drug Interactions

The administration of local anesthetic solutions containing epinephrine or norepinephrine to patients receiving monoamine oxidase inhibitors or tricyclic antidepressants may produce severe, prolonged hypertension.
Phenothiazines and butyrophenones may reduce or reverse the pressor effect of epinephrine.
Concurrent use of these agents should generally be avoided. In situations when concurrent therapy is necessary, careful patient monitoring is essential.
Concurrent administration of vasopressor drugs (for the treatment of hypotension related to obstetric blocks) and ergot-type oxytocic drugs may cause severe, persistent hypertension or cerebrovascular accidents.

Drug/Laboratory Test Interactions

The intramuscular injection of lidocaine hydrochloride may result in an increase in creatine phosphokinase levels. Thus, the use of this enzyme determination, without isoenzyme separation, as a diagnostic test for the presence of acute myocardial infarction may be compromised by the intramuscular injection of lidocaine hydrochloride.
Patients who are administered local anesthetics are at increased risk of developing methemoglobinemia when concurrently exposed to the following drugs, which could include other local anesthetics:
Examples of Drugs Associated with Methemoglobinemia:

Class | Examples
Nitrates/Nitrites | nitric oxide, nitroglycerin, nitroprusside, nitrous oxide
Local anesthetics | articaine, benzocaine, bupivacaine, lidocaine, mepivacaine, prilocaine, procaine, ropivacaine, tetracaine
Antineoplastic agents | cyclophosphamide, flutamide, hydroxyurea, ifosfamide, rasburicase
Antibiotics | dapsone, nitrofurantoin, para-aminosalicylic acid, sulfonamides
Antimalarials | chloroquine, primaquine
Anticonvulsants | Phenobarbital, phenytoin, sodium valproate
Other drugs | acetaminophen, metoclopramide, quinine, sulfasalazine

Carcinogenesis, Mutagenesis, Impairment of Fertility

Studies of lidocaine hydrochloride in animals to evaluate the carcinogenic and mutagenic potential or the effect on fertility have not been conducted.

Pregnancy

Teratogenic Effects

Reproduction studies have been performed in rats at doses up to 6.6 times the human dose and have revealed no evidence of harm to the fetus caused by lidocaine hydrochloride. There are, however, no adequate and well-controlled studies in pregnant women. Animal reproduction studies are not always predictive of human response. General consideration should be given to this fact before administering lidocaine hydrochloride to women of childbearing potential, especially during early pregnancy when maximum organogenesis takes place.

Labor and Delivery

Local anesthetics rapidly cross the placenta and when used for epidural, paracervical, pudendal or caudal block anesthesia, can cause varying degrees of maternal, fetal and neonatal toxicity see CLINICAL PHARMACOLOGY, Pharmacokinetics and Metabolism). The potential for toxicity depends upon the procedure performed, the type and amount of drug used, and the technique of drug administration. Adverse reactions in the parturient, fetus and neonate involve alterations of the central nervous system, peripheral vascular tone and cardiac function.
Maternal hypotension has resulted from regional anesthesia. Local anesthetics produce vasodilation by blocking sympathetic nerves. Elevating the patient’s legs and positioning her on her left side will help prevent decreases in blood pressure.
The fetal heart rate also should be monitored continuously, and electronic fetal monitoring is highly advisable.
Epidural, spinal, paracervical, or pudendal anesthesia may alter the forces of parturition through changes in uterine contractility or maternal expulsive efforts. In one study, paracervical block anesthesia was associated with a decrease in the mean duration of first stage labor and facilitation of cervical dilation. However, spinal and epidural anesthesia have also been reported to prolong the second stage of labor by removing the parturient’s reflex urge to bear down or by interfering with motor function. The use of obstetrical anesthesia may increase the need for forceps assistance.
The use of some local anesthetic drug products during labor and delivery may be followed by diminished muscle strength and tone for the first day or two of life. The long-term significance of these observations is unknown. Fetal bradycardia may occur in 20 to 30 percent of patients receiving paracervical nerve block anesthesia with the amide-type local anesthetics and may be associated with fetal acidosis. Fetal heart rate should always be monitored during paracervical anesthesia. The physician should weigh the possible advantages against risks when considering a paracervical block in prematurity, toxemia of pregnancy, and fetal distress. Careful adherence to recommended dosage is of the utmost importance in obstetrical paracervical block. Failure to achieve adequate analgesia with recommended doses should arouse suspicion of intravascular or fetal intracranial injection. Cases compatible with unintended fetal intracranial injection of local anesthetic solution have been reported following intended paracervical or pudendal block or both. Babies so affected present with unexplained neonatal depression at birth, which correlates with high local anesthetic serum levels, and often manifest seizures within six hours. Prompt use of supportive measures combined with forced urinary excretion of the local anesthetic has been used successfully to manage this complication.
Case reports of maternal convulsions and cardiovascular collapse following use of some local anesthetics for paracervical block in early pregnancy (as anesthesia for elective abortion) suggest that systemic absorption under these circumstances may be rapid. The recommended maximum dose of each drug should not be exceeded. Injection should be made slowly and with frequent aspiration. Allow a 5-minute interval between sides.

Nursing Mothers

It is not known whether this drug is excreted in human milk. Because many drugs are excreted in human milk, caution should be exercised when lidocaine hydrochloride is administered to a nursing woman.

Pediatric Use

Dosages in children should be reduced, commensurate with age, body weight and physical condition, see DOSAGE AND ADMINISTRATION.

ADVERSE REACTIONS

Systemic

Adverse experiences following the administration of lidocaine hydrochloride are similar in nature to those observed with other amide local anesthetic agents. These adverse experiences are, in general, dose-related and may result from high plasma levels caused by excessive dosage, rapid absorption or inadvertent intravascular injection, or may result from a hypersensitivity, idiosyncrasy or diminished tolerance on the part of the patient. Serious adverse experiences are generally systemic in nature. The following types are those most commonly reported:

Central Nervous System

CNS manifestations are excitatory and/or depressant and may be characterized by lightheadedness, nervousness, apprehension, euphoria, confusion, dizziness, drowsiness, tinnitus, blurred or double vision, vomiting, sensations of heat, cold or numbness, twitching, tremors, convulsions, unconsciousness, respiratory depression and arrest. The excitatory manifestations may be very brief or may not occur at all, in which case the first manifestation of toxicity may be drowsiness merging into unconsciousness and respiratory arrest.

Drowsiness following the administration of lidocaine hydrochloride is usually an early sign of a high blood level of the drug and may occur as a consequence of rapid absorption.

Cardiovascular System

Cardiovascular manifestations are usually depressant and are characterized by bradycardia, hypotension, and cardiovascular collapse, which may lead to cardiac arrest.

Allergic

Allergic reactions are characterized by cutaneous lesions, urticaria, edema or anaphylactoid reactions. Allergic reactions may occur as a result of sensitivity to local anesthetic agents. Allergic reactions, including anaphylactic reactions, may occur as a result of sensitivity to lidocaine, but are infrequent. If allergic reactions do occur, they should be managed by conventional means. The detection of sensitivity by skin testing is of doubtful value.
There have been no reports of cross sensitivity between lidocaine hydrochloride and procainamide or between lidocaine hydrochloride and quinidine.

Neurologic

The incidences of adverse reactions associated with the use of local anesthetics may be related to the total dose of local anesthetic administered and are also dependent upon the particular drug used, the route of administration and the physical status of the patient. In a prospective review of 10,440 patients who received lidocaine hydrochloride for spinal anesthesia, the incidences of adverse reactions were reported to be about 3 percent each for positional headaches, hypotension and backache; 2 percent for shivering; and less than 1 percent each for peripheral nerve symptoms, nausea, respiratory inadequacy and double vision. Many of these observations may be related to local anesthetic techniques, with or without a contribution from the local anesthetic.
In the practice of caudal or lumbar epidural block, occasional unintentional penetration of the subarachnoid space by the catheter may occur. Subsequent adverse effects may depend partially on the amount of drug administered subdurally. These may include spinal block of varying magnitude (including total spinal block), hypotension secondary to spinal block, loss of bladder and bowel control, and loss of perineal sensation and sexual function. Persistent motor, sensory and/or autonomic (sphincter control) deficit of some lower spinal segments with slow recovery (several months) or incomplete recovery have been reported in rare instances when caudal or lumbar epidural block has been attempted. Backache and headache have also been noted following use of these anesthetic procedures.
There have been reported cases of permanent injury to extraocular muscles requiring surgical repair following retrobulbar administration.

Hematologic

Methemoglobinemia.

OVERDOSAGE

Acute emergencies from local anesthetics are generally related to high plasma levels encountered during therapeutic use of local anesthetics or to unintended subarachnoid injection of local anesthetic solution (see ADVERSE REACTIONS, WARNINGS, and PRECAUTIONS).

Management of Local Anesthetic Emergencies

The first consideration is prevention, best accomplished by careful and constant monitoring of cardiovascular and respiratory vital signs and the patient’s state of consciousness after each local anesthetic injection. At the first sign of change, oxygen should be administered.
The first step in the management of convulsions, as well as underventilation or apnea due to unintended subarachnoid injection of drug solution, consists of immediate attention to the maintenance of a patent airway and assisted or controlled ventilation with oxygen and a delivery system capable of permitting immediate positive airway pressure by mask. Immediately after the institution of these ventilatory measures, the adequacy of the circulation should be evaluated, keeping in mind that drugs used to treat convulsions sometimes depress the circulation when administered intravenously. Should convulsions persist despite adequate respiratory support, and if the status of the circulation permits, small increments of an ultra-short acting barbiturate (such as thiopental or thiamylal) or a benzodiazepine (such as diazepam) may be administered intravenously. The clinician should be familiar, prior to the use of local anesthetics, with these anticonvulsant drugs. Supportive treatment of circulatory depression may require administration of intravenous fluids and, when appropriate, a vasopressor as directed by the clinical situation (e.g., ephedrine).
If not treated immediately, both convulsions and cardiovascular depression can result in hypoxia, acidosis, bradycardia, arrhythmias and cardiac arrest. Underventilation or apnea due to unintentional subarachnoid injection of local anesthetic solution may produce these same signs and also lead to cardiac arrest if ventilatory support is not instituted. If cardiac arrest should occur, standard cardiopulmonary resuscitative measures should be instituted.
Endotracheal intubation, employing drugs and techniques familiar to the clinician, may be indicated, after initial administration of oxygen by mask, if difficulty is encountered in the maintenance of a patent airway or if prolonged ventilatory support (assisted or controlled) is indicated.
Dialysis is of negligible value in the treatment of acute overdosage with lidocaine hydrochloride.
The oral LD50 of lidocaine hydrochloride in non-fasted female rats is 459 (346 to 773) mg/kg (as the salt) and 214 (159 to 324) mg/kg (as the salt) in fasted female rats.

DOSAGE AND ADMINISTRATION

Table 1 (Recommended Dosages) summarizes the recommended volumes and concentrations of lidocaine hydrochloride injection for various types of anesthetic procedures. The dosages suggested in this table are for normal healthy adults and refer to the use of epinephrine-free solutions. When larger volumes are required, only solutions containing epinephrine should be used except in those cases where vasopressor drugs may be contraindicated.

There have been adverse event reports of chondrolysis in patients receiving intra-articular infusions of local anesthetics following arthroscopic and other surgical procedures. Lidocaine hydrochloride injection is not approved for this use (see WARNINGSand DOSAGE AND ADMINISTRATION).
These recommended doses serve only as a guide to the amount of anesthetic required for most routine procedures. The actual volumes and concentrations to be used depend on a number of factors such as type and extent of surgical procedure, depth of anesthesia and degree of muscular relaxation required, duration of anesthesia required, and the physical condition of the patient. In all cases the lowest concentration and smallest dose that will produce the desired result should be given. Dosages should be reduced for children and for the elderly and debilitated patients and patients with cardiac and/or liver disease.
The onset of anesthesia, the duration of anesthesia and the degree of muscular relaxation are proportional to the volume and concentration (i.e., total dose) of local anesthetic used. Thus, an increase in volume and concentration of lidocaine hydrochloride injection will decrease the onset of anesthesia, prolong the duration of anesthesia, provide a greater degree of muscular relaxation and increase the segmental spread of anesthesia. However, increasing the volume and concentration of lidocaine hydrochloride injection may result in a more profound fall in blood pressure when used in epidural anesthesia. Although the incidence of side effects with lidocaine hydrochloride is quite low, caution should be exercised when employing large volumes and concentrations, since the incidence of side effects is directly proportional to the total dose of local anesthetic agent injected.

Epidural Anesthesia

For epidural anesthesia, only the following dosage forms of lidocaine hydrochloride injection are recommended:
1% without epinephrine 5 mL ampules
2% without epinephrine 2 mL ampules
Although these solutions are intended specifically for epidural anesthesia, they may also be used for infiltration and peripheral nerve block, provided they are employed as single dose units. These solutions contain no bacteriostatic agent.
In epidural anesthesia, the dosage varies with the number of dermatomes to be anesthetized (generally 2 to 3 mL of the indicated concentration per dermatome).

Caudal and Lumbar Epidural Block

As a precaution against the adverse experience sometimes observed following unintentional penetration of the subarachnoid space, a test dose such as 2 to 3 mL of 1.5% lidocaine hydrochloride should be administered at least 5 minutes prior to injecting the total volume required for a lumbar or caudal epidural block. The test dose should be repeated if the patient is moved in a manner that may have displaced the catheter. Epinephrine, if contained in the test dose (10 to 15 mcg have been suggested), may serve as a warning of unintentional intravascular injection. If injected into a blood vessel, this amount of epinephrine is likely to produce a transient “epinephrine response” within 45 seconds, consisting of an increase in heart rate and systolic blood pressure, circumoral pallor, palpitations and nervousness in the unsedated patient. The sedated patient may exhibit only a pulse rate increase of 20 or more beats per minute for 15 or more seconds. Patients on beta blockers may not manifest changes in heart rate, but blood pressure monitoring can detect an evanescent rise in systolic blood pressure. Adequate time should be allowed for onset of anesthesia after administration of each test dose. The rapid injection of a large volume of lidocaine hydrochloride injection through the catheter should be avoided, and, when feasible, fractional doses should be administered.
In the event of the known injection of a large volume of local anesthetic solution into the subarachnoid space, after suitable resuscitation and if the catheter is in place, consider attempting the recovery of drug by draining a moderate amount of cerebrospinal fluid (such as 10 mL) through the epidural catheter.

MAXIMUM RECOMMENDED DOSAGES

Adults

For normal healthy adults, the maximum individual dose should not exceed 4.5 mg/kg (2 mg/lb) of body weight, and in general it is recom mended that the max i m um t otal dose does not exceed 300 mg. For continuous epidural or caudal anesthesia, the maximum recommended dosage should not be administered at intervals of less than 90 minutes. When continuous lumbar or caudal epidural anesthesia is used for non-obstetrical procedures, more drug may be administered if required to produce adequate anesthesia.
The maximum recommended dose per 90 minute period of lidocaine hydrochloride for paracervical block in obstetrical patients and non-obstetrical patients is 200 mg total. One half of the total dose is usually administered to each side. Inject slowly, five minutes between sides (see also discussion of paracervical block in PRECAUTIONS).
For intravenous regional anesthesia, the dose administered should not exceed 4 mg/kg in adults.

Children

It is difficult to recommend a maximum dose of any drug for children, since this varies as a function of age and weight. For children over 3 years of age who have a normal lean body mass and normal body development, the maximum dose is determined by the child’s age and weight. For example, in a child of 5 years weighing 50 lbs the dose of lidocaine hydrochloride should not exceed 75 to 100 mg (1.5 to 2 mg/lb). The use of even more dilute solutions (i.e., 0.25 to 0.5%) and total dosages not to exceed 3 mg/kg (1.4 mg/lb) are recommended for induction of intravenous regional anesthesia in children.
In order to guard against systemic toxicity, the lowest effective concentration and lowest effective dose should be used at all times. In some cases it will be necessary to dilute available concentrations with 0.9% sodium chloride injection in order to obtain the required final concentration.
NOTE: Parenteral drug products should be inspected visually for particulate matter and discoloration prior to administration whenever the solution and container permit. Do not use if solution is discolored or contains a precipitate.

Table 1: Recommended Dosages
Procedure | Lidocaine Hydrochloride Injection (without epinephrine)
Procedure | Conc (%) | Vol (mL) | Total Dose (mg)
Infiltration
Percutaneous | 0.5 or 1 | 1 to 60 | 5 to 300
Intravenous regional | 0.5 | 10 to 60 | 50 to 300
Peripheral Nerve Blocks, e.g.,
Brachial | 1.5 | 15 to 20 | 225 to 300
Dental | 2 | 1 to 5 | 20 to 100
Intercostal | 1 | 3 | 30
Paravertebral | 1 | 3 to 5 | 30 to 50
Pudendal (each side) | 1 | 10 | 100
Paracervical
Obstetrical analgesia (each side) | 1 | 10 | 100
Sympathetic Nerve Blocks, e.g.,
Cervical (stellate ganglion) | 1 | 5 | 50
Lumbar | 1 | 5 to 10 | 50 to 100
Central Neural Blocks
Epidural*
Thoracic | 1 | 20 to 30 | 200 to 300
Lumbar
Analgesia | 1 | 25 to 30 | 250 to 300
Anesthesia | 1.5 | 15 to 20 | 225 to 300
 | 2 | 10 to 15 | 200 to 300
Caudal
Obstetrical analgesia | 1 | 20 to 30 | 200 to 300
Surgical anesthesia | 1.5 | 15 to 20 | 225 to 300
*Dose determined by number of dermatomes to be anesthetized (2 to 3 mL/dermatome).

THE ABOVE SUGGESTED CONCENTRATIONS AND VOLUMES SERVE ONLY AS A GUIDE. OTHER VOLUMES AND CONCENTRATIONS MAY BE USED PROVIDED THE TOTAL MAXIMUM RECOMMENDED DOSE IS NOT EXCEEDED.

STERILIZATION, STORAGE AND TECHNICAL PROCEDURES

Disinfecting agents containing heavy metals, which cause release of respective ions (mercury, zinc, copper, etc.) should not be used for skin or mucous membrane disinfection as they have been related to incidents of swelling and edema.

HOW SUPPLIED

Lidocaine Hydrochloride Injection USP, is supplied as follows:
Lidocaine Hydrochloride Injection USP, 1% (10 mg/mL)
2 mL Ampules in a Carton of 10 NDC 55150-158-72
Sterile, Nonpyrogenic
Discard unused portion.
Store at 20° to 25°C (68° to 77°F) [see USP Controlled Room Temperature].
Distributed by:
AuroMedics Pharma LLC
279 Princeton-Hightstown Rd.
E. Windsor, NJ 08520
Manufactured by:
Eugia Pharma Specialities Limited
Hyderabad - 500032
India
Revised: October 2021

Povidone-Iodine Swabsticks

Active Ingredient Purpose

Povidone Iodine 10% w/v (9.85% w/w/) Antiseptic

Purpose:

- First aid antiseptic to help prevent skin infection in minor cuts, scrapes and burns.
- For preparation of the skin prior to surgery.
- Helps reduce bacteria that can potentially cause skin infections.

Warnings:

Section Text

- FOR EXTERNAL USE ONLY

Do not use:

- As a first aid antiseptic for more than 1 week.
- In the eyes.
- Over large areas of the body.

Ask a doctor before use if you have:

- Deep puncture wounds
- Animal bites
- Serious burns

Stop Use:

- If irritation and redness develop
- If condition persists for more than 72 hours, consult a physician.

Keep out of reach of children.If swallowed, get medical help or contact a Poison Control Center.

Directions Povidone iodine:

Tear at notch, remove applicator, use only once.

As a first aid antiseptic

- clean affected area
- apply 1 to 3 times daily
- may be covered with a sterile bandage, if bandaged let dry.

For preoperative patient skin preparation

- clean area
- apply to operative site prior to surgery using the applicator

Other information:

Store at room temperature.

Avoid excessive heat

INDICATIONS AND USAGE

For use as an

- first aid antiseptic
- pre-operative skin preperation

Inactive Ingredients

Inactive ingredients: Citric acid, glycerin, polysorbate 80, sodium citrate USP, sodium phosphate dibasic, water

Isopropyl Alcohol 70% Prep Pads

Active ingredient

Isopropyl Alcohol 70% v/v

Purpose

Antiseptic

Uses

For first aid to decrease germs in

- minor cuts
- scrapes
- burns

For preparation of the skin prior to injection

Warnings

For external use only

Flammable - keep away from fire or flame

Do not use

with electrocautery procedures

When using this product do not

- get into eyes
- apply over large areas of the body
- in case of deep or puncture wounds, animal bites or serious burns consult a doctor

Stop use and ask a doctor if

- condition persists or gets worse or lasts for more than 72 hours
- do not use longer than 1 week unless directed by a doctor

Keep out of reach of children.

If swallowed, get medical help or contact a Poison Control Center right away.

Directions

- apply to skin as needed
- discard after single use

Other information

Protect from freezing and avoid excessive heat

Inactive ingredient

Water

PACKAGE LABEL

PRNCIPAL DISPLAY PANEL

NDC: 76420-767-01

RX Only

Dexlido™

Kit Contains

1 Dexamethasone Sodium Phosphate Inj., USP 10mg/mL (1mL)

1 Lidocaine HCl Injection, USP 1% Ampule (2mL)

1 Povidone-Iodine Swabsticks (3 Swabs)

2 Isopropyl Alcohol 70% Prep Pads

1 Pair Nitrile Powder Free Sterile Gloves (M)

1 Drape

1 Adhesive Bandage

5 Non Sterile 4x4 Gauze

Needles and Syringes Not Included

1 Dose

Single Use Only

Distributed by:

Enovachem™

PHARMACEUTICALS

Torrance, CA 90501